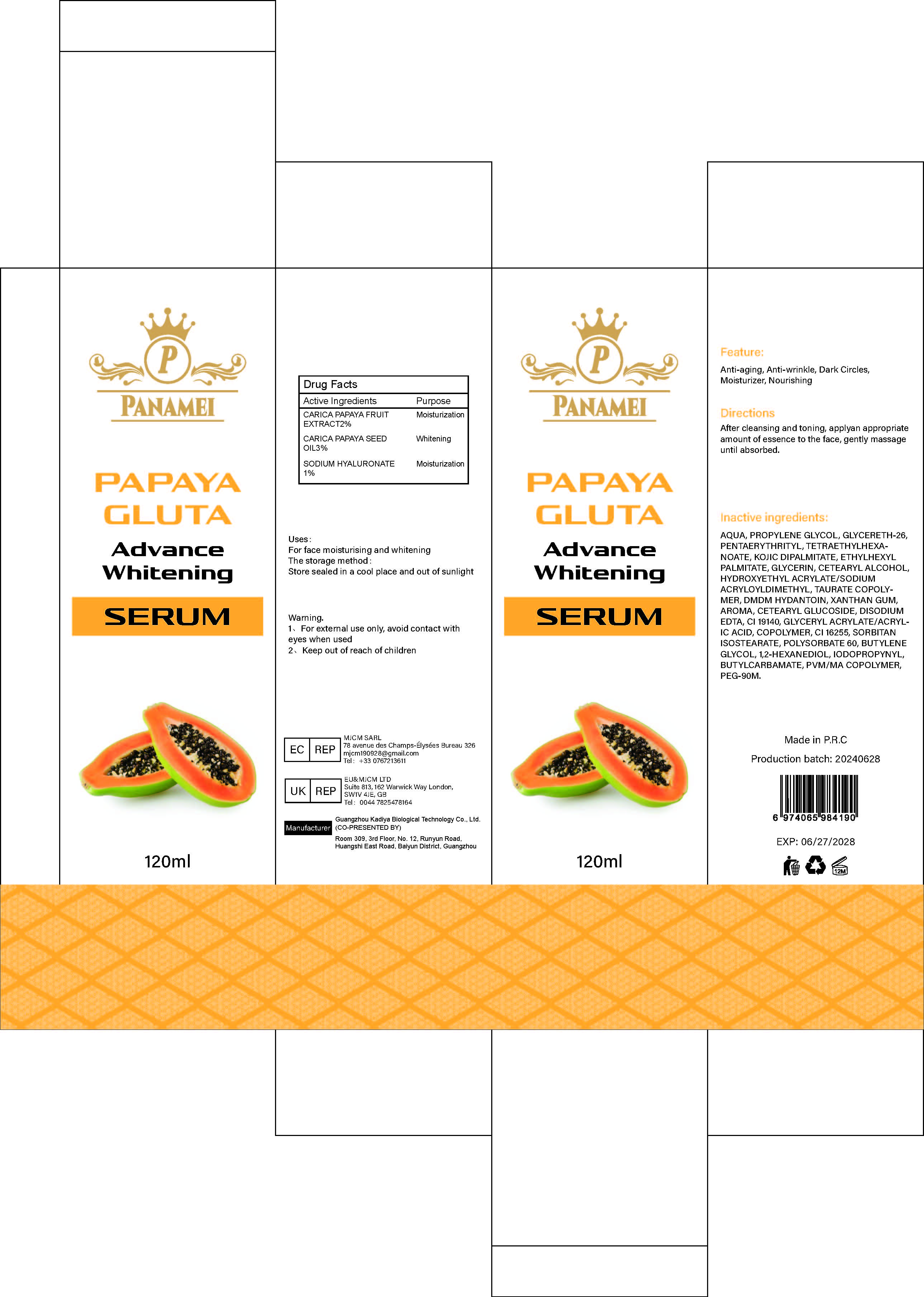 DRUG LABEL: PAPAYA GLUTA Advance Whitening SERUM
NDC: 84423-015 | Form: LIQUID
Manufacturer: Guangzhou Kadiya Biotechnology Co., Ltd.
Category: otc | Type: HUMAN OTC DRUG LABEL
Date: 20240708

ACTIVE INGREDIENTS: PAPAYA SEED OIL 3.6 mg/120 mg
INACTIVE INGREDIENTS: FD&C YELLOW NO. 5; CETOSTEARYL ALCOHOL; DMDM HYDANTOIN; ETHYLHEXYL PALMITATE; EDETATE DISODIUM; BUTYLENE GLYCOL; PENTAERYTHRITYL TETRAETHYLHEXANOATE; IODOPROPYNYL BUTYLCARBAMATE; 1,2-HEXANEDIOL; HYDROXYETHYL ACRYLATE/SODIUM ACRYLOYLDIMETHYL TAURATE COPOLYMER (45000 MPA.S AT 1%); CETEARYL GLUCOSIDE; POLYETHYLENE GLYCOL 4000000; PONCEAU 4R; WATER; GLYCERETH-26; XANTHAN GUM; POLYSORBATE 60; KOJIC DIPALMITATE; GLYCERIN; SORBITAN ISOSTEARATE; METHYL VINYL ETHER AND MALEIC ANHYDRIDE COPOLYMER (1100000 WAMW); PROPYLENE GLYCOL

PURPOSE

Uses:For face moisturising and whitening

INACTIVE INGREDIENT

AQUA、PROPYLENE GLYCOL、GLYCERETH-26、PENTAERYTHRITYL、TETRAETHYLHEXANOATE、KOJIC DIPALMITATE、ETHYLHEXYL PALMITATE、GLYCERIN、CETEARYL ALCOHOL、HYDROXYETHYL ACRYLATE/SODIUM ACRYLOYLDIMETHYL、TAURATE COPOLYMER、DMDM HYDANTOIN、XANTHAN GUM、AROMA、CETEARYL GLUCOSIDE、DISODIUM EDTA、CI 19140、GLYCERYL ACRYLATE/ACRYLIC ACID、COPOLYMER、CI 16255、SORBITAN ISOSTEARATE、POLYSORBATE 60、BUTYLENE GLYCOL、1,2-HEXANEDIOL、IODOPROPYNYL、BUTYLCARBAMATE、PVM/MA COPOLYMER、PEG-90M

Warning.
1、For external use only, avoid contact with eyes when used
2、Keep out of reach of children

INDICATIONS AND USAGE

Anti-aging, Anti-wrinkle, Dark Circles,Moisturizer, Nourishing

KEEP OUT OF REACH OF CHILDREN SECTION

Active Ingredients
CARICA PAPAYA FRUIT EXTRACT 2%
CARICA PAPAYA SEED OIL 3%
SODIUM HYALURONATE 1%

DOSAGE AND ADMINISTRATION

After cleansing and toning, applyan appropriateamount of essence to the face, gently massageuntil absorbed.

PACKAGE LABEL

Active Ingredients
CARICA PAPAYA FRUIT EXTRACT 2%
CARICA PAPAYA SEED OIL 3%
SODIUM HYALURONATE 1%

Uses：
For face moisturising and whitening
Indications: For face moisturising and whitening
The storage method：
Store sealed in a cool place and out of sunlight

Warning.
1、For external use only, avoid contact with eyes when used
2、Keep out of reach of children

Inactive ingredients：
AQUA、PROPYLENE GLYCOL、GLYCERETH-26、PENTAERYTHRITYL、TETRAETHYLHEXANOATE、KOJIC DIPALMITATE、ETHYLHEXYL PALMITATE、GLYCERIN、CETEARYL ALCOHOL、HYDROXYETHYL ACRYLATE/SODIUM ACRYLOYLDIMETHYL、TAURATE COPOLYMER、DMDM HYDANTOIN、XANTHAN GUM、AROMA、CETEARYL GLUCOSIDE、DISODIUM EDTA、CI 19140、GLYCERYL ACRYLATE/ACRYLIC ACID、COPOLYMER、CI 16255、SORBITAN ISOSTEARATE、POLYSORBATE 60、BUTYLENE GLYCOL、1,2-HEXANEDIOL、IODOPROPYNYL、BUTYLCARBAMATE、PVM/MA COPOLYMER、PEG-90M